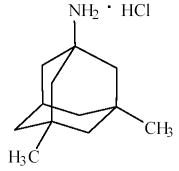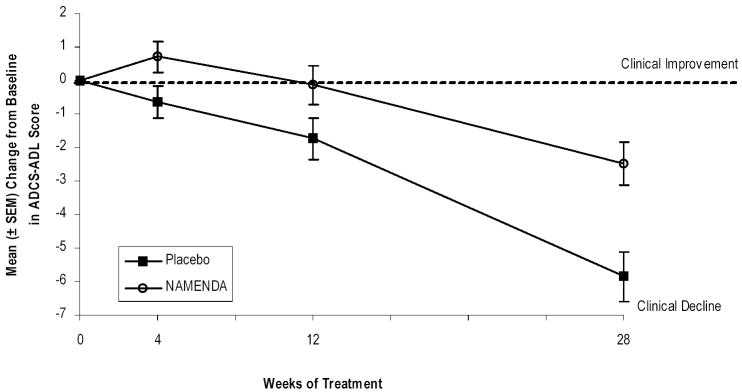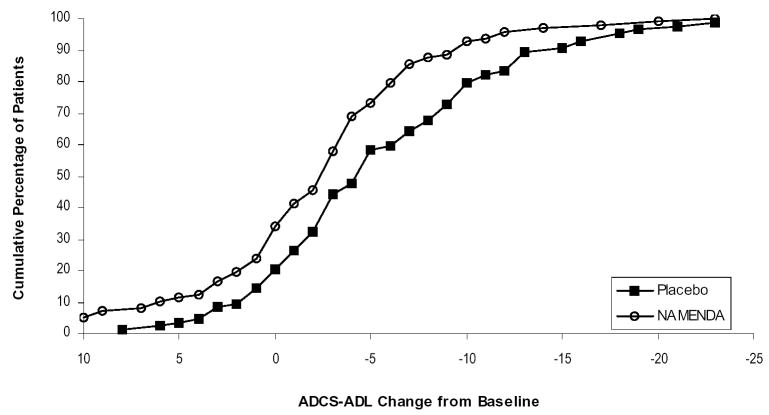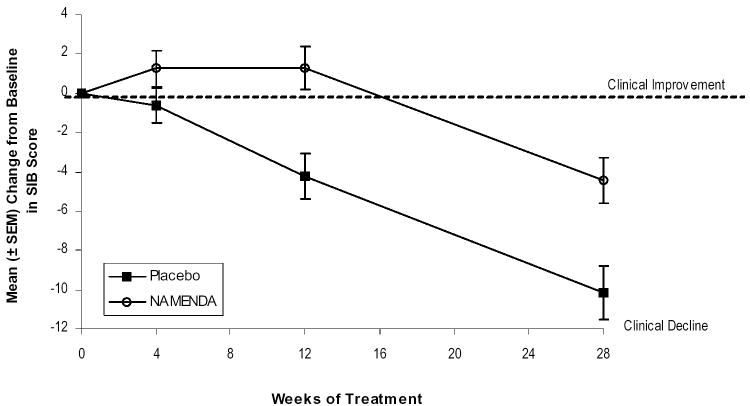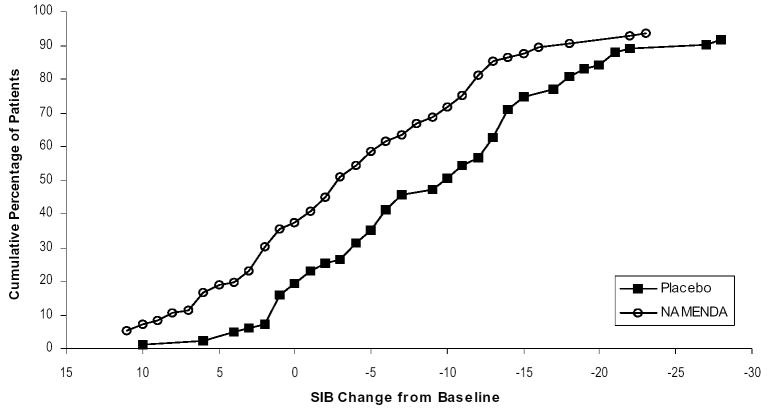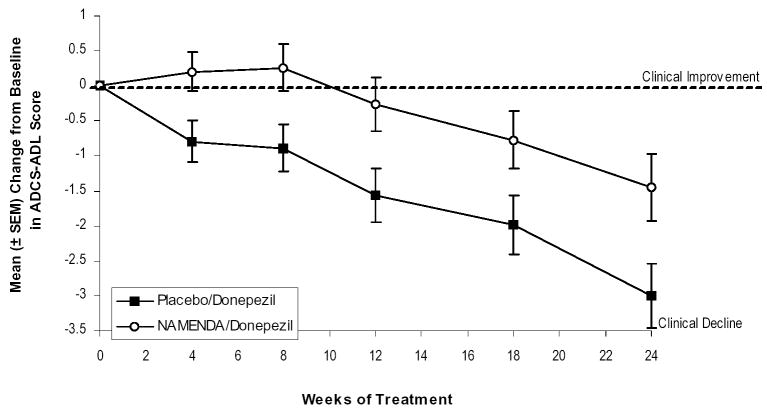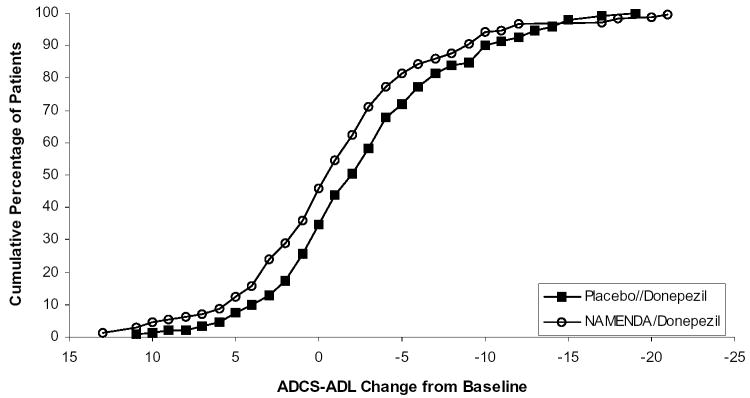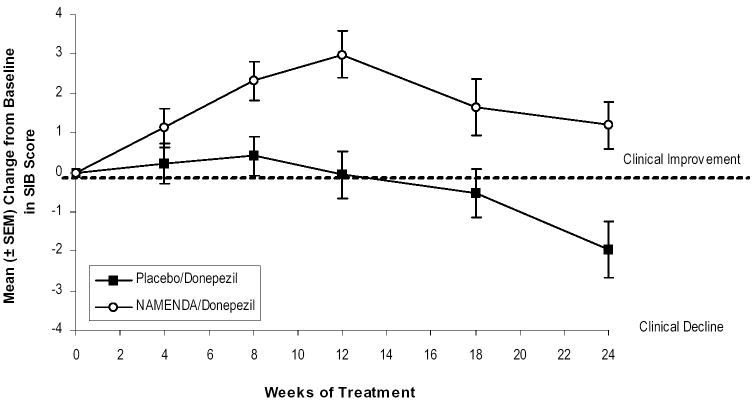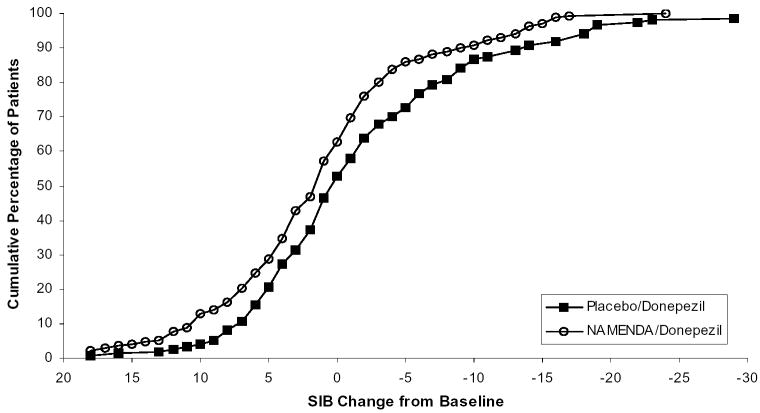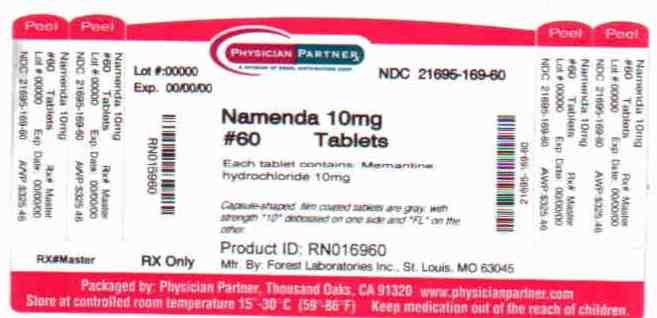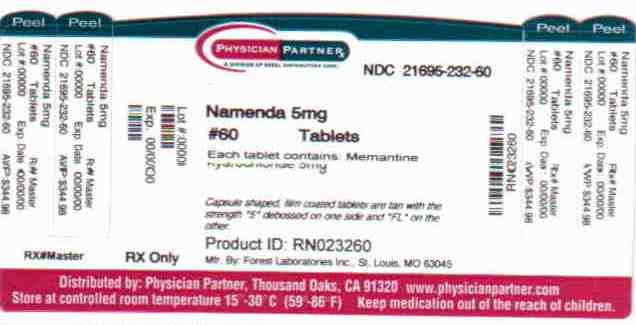 DRUG LABEL: Namenda
NDC: 21695-232 | Form: TABLET
Manufacturer: Rebel Distributors Corp
Category: prescription | Type: HUMAN PRESCRIPTION DRUG LABEL
Date: 20101229

ACTIVE INGREDIENTS: MEMANTINE HYDROCHLORIDE 5 mg/1 1
INACTIVE INGREDIENTS: CELLULOSE, MICROCRYSTALLINE; SILICON DIOXIDE; TALC; CROSCARMELLOSE SODIUM; MAGNESIUM STEARATE; HYPROMELLOSES; TITANIUM DIOXIDE; POLYETHYLENE GLYCOL 400; FD&C YELLOW NO. 6; FD&C BLUE NO. 2

Namenda

Rx Only

DESCRIPTION

Namenda® (memantine hydrochloride) is an orally active NMDA receptor antagonist. The chemical name for memantine hydrochloride is 1-amino-3,5-dimethyladamantane hydrochloride with the following structural formula:

The molecular formula is C12H21N•HCl and the molecular weight is 215.76.

Memantine HCl occurs as a fine white to off-white powder and is soluble in water. Namenda is available as tablets or as an oral solution. Namenda is available for oral administration as capsule-shaped, film-coated tablets containing 5 mg and 10 mg of memantine hydrochloride. The tablets also contain the following inactive ingredients: microcrystalline cellulose/colloidal silicon dioxide, talc, croscarmellose sodium, and magnesium stearate. In addition the following inactive ingredients are also present as components of the film coat: hypromellose, titanium dioxide, polyethylene glycol 400, FD&C yellow #6 and FD&C blue #2 (5 mg tablets), and hypromellose, titanium dioxide, macrogol/polyethylene glycol 400 and iron oxide black (10 mg tablets). Namenda oral solution contains memantine hydrochloride in a strength equivalent to 2 mg of memantine hydrochloride in each mL. The oral solution also contains the following inactive ingredients: sorbitol solution (70%), methyl paraben, propylparaben, propylene glycol, glycerin, natural peppermint flavor #104, citric acid, sodium citrate, and purified water.

CLINICAL PHARMACOLOGY

Mechanism of Action and Pharmacodynamics

Persistent activation of central nervous system N-methyl-D-aspartate (NMDA) receptors by the excitatory amino acid glutamate has been hypothesized to contribute to the symptomatology of Alzheimer's disease. Memantine is postulated to exert its therapeutic effect through its action as a low to moderate affinity uncompetitive (open-channel) NMDA receptor antagonist which binds preferentially to the NMDA receptor-operated cation channels. There is no evidence that memantine prevents or slows neurodegeneration in patients with Alzheimer's disease.

Memantine showed low to negligible affinity for GABA, benzodiazepine, dopamine, adrenergic, histamine and glycine receptors and for voltage-dependent Ca^2+, Na^+ or K^+ channels. Memantine also showed antagonistic effects at the 5HT3 receptor with a potency similar to that for the NMDA receptor and blocked nicotinic acetylcholine receptors with one-sixth to one-tenth the potency.

In vitro studies have shown that memantine does not affect the reversible inhibition of acetylcholinesterase by donepezil, galantamine, or tacrine.

Pharmacokinetics

Memantine is well absorbed after oral administration and has linear pharmacokinetics over the therapeutic dose range. It is excreted predominantly in the urine, unchanged, and has a terminal elimination half life of about 60-80 hours.

Absorption and Distribution

Following oral administration memantine is highly absorbed with peak concentrations reached in about 3-7 hours. Food has no effect on the absorption of memantine. The mean volume of distribution of memantine is 9-11 L/kg and the plasma protein binding is low (45%).

Metabolism and Elimination

Memantine undergoes partial hepatic metabolism. About 48% of administered drug is excreted unchanged in urine; the remainder is converted primarily to three polar metabolites which possess minimal NMDA receptor antagonistic activity: the N-glucuronide conjugate, 6-hydroxy memantine, and 1-nitroso-deaminated memantine. A total of 74% of the administered dose is excreted as the sum of the parent drug and the N-glucuronide conjugate. The hepatic microsomal CYP450 enzyme system does not play a significant role in the metabolism of memantine. Memantine has a terminal elimination half-life of about 60-80 hours. Renal clearance involves active tubular secretion moderated by pH dependent tubular reabsorption.

Special Populations

Renal Impairment: Memantine pharmacokinetics were evaluated following single oral administration of 20 mg memantine HCl in 8 subjects with mild renal impairment (creatinine clearance, CLcr, >50 – 80 mL/min), 8 subjects with moderate renal impairment (CLcr 30 – 49 mL/min), 7 subjects with severe renal impairment (CLcr 5 – 29 mL/min) and 8 healthy subjects (CLcr > 80 mL/min) matched as closely as possible by age, weight and gender to the subjects with renal impairment. Mean AUC0-∞ increased by 4%, 60%, and 115% in subjects with mild, moderate, and severe renal impairment, respectively, compared to healthy subjects. The terminal elimination half-life increased by 18%, 41%, and 95% in subjects with mild, moderate, and severe renal impairment, respectively, compared to healthy subjects.

No dosage adjustment is recommended for patients with mild and moderate renal impairment. Dosage should be reduced in patients with severe renal impairment (See DOSAGE AND ADMINISTRATION).

Hepatic Impairment: Memantine pharmacokinetics were evaluated following the administration of single oral doses of 20 mg in 8 subjects with moderate hepatic impairment (Child-Pugh Class B, score 7-9) and 8 subjects who were age-, gender-, and weight-matched to the hepatically-impaired subjects. There was no change in memantine exposure (based on Cmax and AUC) in subjects with moderate hepatic impairment as compared with healthy subjects. However, terminal elimination half-life increased by about 16% in subjects with moderate hepatic impairment as compared with healthy subjects. No dose adjustment is recommended for patients with mild and moderate hepatic impairment. Memantine should be administered with caution to patients with severe hepatic impairment as the pharmacokinetics of memantine have not been evaluated in that population.

Elderly: The pharmacokinetics of Namenda in young and elderly subjects are similar.

Gender: Following multiple dose administration of Namenda 20 mg b.i.d., females had about 45% higher exposure than males, but there was no difference in exposure when body weight was taken into account.

Drug-Drug Interactions

Substrates of Microsomal Enzymes: In vitro studies indicated that at concentrations exceeding those associated with efficacy, memantine does not induce the cytochrome P450 isozymes CYP1A2, CYP2C9, CYP2E1 and CYP3A4/5. In addition, in vitro studies have shown that memantine produces minimal inhibition of CYP450 enzymes CYP1A2, CYP2A6, CYP2C9, CYP2D6, CYP2E1, and CYP3A4. These data indicate that no pharmacokinetic interactions with drugs metabolized by these enzymes are expected.

Inhibitors of Microsomal Enzymes: Since memantine undergoes minimal metabolism, with the majority of the dose excreted unchanged in urine, an interaction between memantine and drugs that are inhibitors of CYP450 enzymes is unlikely. Coadministration of Namenda with the AChE inhibitor donepezil HCl does not affect the pharmacokinetics of either compound.

Drugs Eliminated via Renal Mechanisms: Memantine is eliminated in part by tubular secretion. In vivo studies have shown that multiple doses of the diuretic hydrochlorothiazide/triamterene (HCTZ/TA) did not affect the AUC of memantine at steady state. Memantine did not affect the bioavailability of TA, and decreased AUC and Cmax of HCTZ by about 20%. Coadministration of memantine with the antihyperglycemic drug Glucovance® (glyburide and metformin HCl) did not affect the pharmacokinetics of memantine, metformin and glyburide. Memantine did not modify the serum glucose lowering effects of Glucovance®, indicating the absence of a pharmacodynamic interaction.

Drugs that make the urine alkaline: The clearance of memantine was reduced by about 80% under alkaline urine conditions at pH 8. Therefore, alterations of urine pH towards the alkaline state may lead to an accumulation of the drug with a possible increase in adverse effects. Drugs that alkalinize the urine (e.g. carbonic anhydrase inhibitors, sodium bicarbonate) would be expected to reduce renal elimination of memantine.

Drugs highly bound to plasma proteins: Because the plasma protein binding of memantine is low (45%), an interaction with drugs that are highly bound to plasma proteins, such as warfarin and digoxin, is unlikely.

CLINICAL TRIALS

The effectiveness of Namenda (memantine hydrochloride) as a treatment for patients with moderate to severe Alzheimer's disease was demonstrated in 2 randomized, double-blind, placebo-controlled clinical studies (Studies 1 and 2) conducted in the United States that assessed both cognitive function and day to day function. The mean age of patients participating in these two trials was 76 with a range of 50-93 years. Approximately 66% of patients were female and 91% of patients were Caucasian.

A third study (Study 3), carried out in Latvia, enrolled patients with severe dementia, but did not assess cognitive function as a planned endpoint.

Study Outcome Measures: In each U.S. study, the effectiveness of Namenda was determined using both an instrument designed to evaluate overall function through caregiver-related assessment, and an instrument that measures cognition. Both studies showed that patients on Namenda experienced significant improvement on both measures compared to placebo.

Day-to-day function was assessed in both studies using the modified Alzheimer's disease Cooperative Study - Activities of Daily Living inventory (ADCS-ADL). The ADCS-ADL consists of a comprehensive battery of ADL questions used to measure the functional capabilities of patients. Each ADL item is rated from the highest level of independent performance to complete loss. The investigator performs the inventory by interviewing a caregiver familiar with the behavior of the patient. A subset of 19 items, including ratings of the patient's ability to eat, dress, bathe, telephone, travel, shop, and perform other household chores has been validated for the assessment of patients with moderate to severe dementia. This is the modified ADCS-ADL, which has a scoring range of 0 to 54, with the lower scores indicating greater functional impairment.

The ability of Namenda to improve cognitive performance was assessed in both studies with the Severe Impairment Battery (SIB), a multi-item instrument that has been validated for the evaluation of cognitive function in patients with moderate to severe dementia. The SIB examines selected aspects of cognitive performance, including elements of attention, orientation, language, memory, visuospatial ability, construction, praxis, and social interaction. The SIB scoring range is from 0 to 100, with lower scores indicating greater cognitive impairment.

Study 1 (Twenty-Eight-Week Study)

In a study of 28 weeks duration, 252 patients with moderate to severe probable Alzheimer's disease (diagnosed by DSM-IV and NINCDS-ADRDA criteria, with Mini-Mental State Examination scores ≥3 and ≤14 and Global Deterioration Scale Stages 5-6) were randomized to Namenda or placebo. For patients randomized to Namenda, treatment was initiated at 5 mg once daily and increased weekly by 5 mg/day in divided doses to a dose of 20 mg/day (10 mg twice a day).

Effects on the ADCS-ADL:

Figure 1 shows the time course for the change from baseline in the ADCS-ADL score for patients in the two treatment groups completing the 28 weeks of the study. At 28 weeks of treatment, the mean difference in the ADCS-ADL change scores for the Namenda -treated patients compared to the patients on placebo was 3.4 units. Using an analysis based on all patients and carrying their last study observation forward (LOCF analysis), Namenda treatment was statistically significantly superior to placebo.

Figure 1: Time course of the change from baseline in ADCS-ADL score for patients completing 28 weeks of treatment.

Figure 2 shows the cumulative percentages of patients from each of the treatment groups who had attained at least the change in the ADCS-ADL shown on the X axis.

The curves show that both patients assigned to Namenda and placebo have a wide range of responses and generally show deterioration (a negative change in ADCS-ADL compared to baseline), but that the Namenda group is more likely to show a smaller decline or an improvement. (In a cumulative distribution display, a curve for an effective treatment would be shifted to the left of the curve for placebo, while an ineffective or deleterious treatment would be superimposed upon or shifted to the right of the curve for placebo.)

Figure 2: Cumulative percentage of patients completing 28 weeks of double-blind treatment with specified changes from baseline in ADCS-ADL scores.

Effects on the SIB:

Figure 3 shows the time course for the change from baseline in SIB score for the two treatment groups over the 28 weeks of the study. At 28 weeks of treatment, the mean difference in the SIB change scores for the Namenda-treated patients compared to the patients on placebo was 5.7 units. Using an LOCF analysis, Namenda treatment was statistically significantly superior to placebo.

Figure 3: Time course of the change from baseline in SIB score for patients completing 28 weeks of treatment.

Figure 4 shows the cumulative percentages of patients from each treatment group who had attained at least the measure of change in SIB score shown on the X axis.

The curves show that both patients assigned to Namenda and placebo have a wide range of responses and generally show deterioration, but that the Namenda group is more likely to show a smaller decline or an improvement.

Figure 4: Cumulative percentage of patients completing 28 weeks of double-blind treatment with specified changes from baseline in SIB scores.

Study 2 (Twenty-Four-Week Study)

In a study of 24 weeks duration, 404 patients with moderate to severe probable Alzheimer's disease (diagnosed by NINCDS-ADRDA criteria, with Mini-Mental State Examination scores ≥5 and ≤14) who had been treated with donepezil for at least 6 months and who had been on a stable dose of donepezil for the last 3 months were randomized to Namenda or placebo while still receiving donepezil. For patients randomized to Namenda, treatment was initiated at 5 mg once daily and increased weekly by 5 mg/day in divided doses to a dose of 20 mg/day (10 mg twice a day).

Effects on the ADCS-ADL:

Figure 5 shows the time course for the change from baseline in the ADCS-ADL score for the two treatment groups over the 24 weeks of the study. At 24 weeks of treatment, the mean difference in the ADCS-ADL change scores for the Namenda/donepezil treated patients (combination therapy) compared to the patients on placebo/donepezil (monotherapy) was 1.6 units. Using an LOCF analysis, Namenda/donepezil treatment was statistically significantly superior to placebo/donepezil.

Figure 5: Time course of the change from baseline in ADCS-ADL score for patients completing 24 weeks of treatment.

Figure 6 shows the cumulative percentages of patients from each of the treatment groups who had attained at least the measure of improvement in the ADCS-ADL shown on the X axis.

The curves show that both patients assigned to Namenda/donepezil and placebo/donepezil have a wide range of responses and generally show deterioration, but that the Namenda/donepezil group is more likely to show a smaller decline or an improvement.

Figure 6: Cumulative percentage of patients completing 24 weeks of double-blind treatment with specified changes from baseline in ADCS-ADL scores.

Effects on the SIB:

Figure 7 shows the time course for the change from baseline in SIB score for the two treatment groups over the 24 weeks of the study. At 24 weeks of treatment, the mean difference in the SIB change scores for the Namenda/donepezil-treated patients compared to the patients on placebo/donepezil was 3.3 units. Using an LOCF analysis, Namenda/donepezil treatment was statistically significantly superior to placebo/donepezil.

Figure 7: Time course of the change from baseline in SIB score for patients completing 24 weeks of treatment.

Figure 8 shows the cumulative percentages of patients from each treatment group who had attained at least the measure of improvement in SIB score shown on the X axis.

The curves show that both patients assigned to Namenda/donepezil and placebo/donepezil have a wide range of responses, but that the Namenda/donepezil group is more likely to show an improvement or a smaller decline.

Figure 8: Cumulative percentage of patients completing 24 weeks of double-blind treatment with specified changes from baseline in SIB scores.

Study 3 (Twelve-Week Study)

In a double-blind study of 12 weeks duration, conducted in nursing homes in Latvia, 166 patients with dementia according to DSM-III-R, a Mini-Mental State Examination score of less than 10, and Global Deterioration Scale staging of 5 to 7 were randomized to either Namenda or placebo. For patients randomized to Namenda, treatment was initiated at 5 mg once daily and increased to 10 mg once daily after 1 week. The primary efficacy measures were the care dependency subscale of the Behavioral Rating Scale for Geriatric Patients (BGP), a measure of day-to-day function, and a Clinical Global Impression of Change (CGI-C), a measure of overall clinical effect. No valid measure of cognitive function was used in this study. A statistically significant treatment difference at 12 weeks that favored Namenda over placebo was seen on both primary efficacy measures. Because the patients entered were a mixture of Alzheimer's disease and vascular dementia, an attempt was made to distinguish the two groups and all patients were later designated as having either vascular dementia or Alzheimer's disease, based on their scores on the Hachinski Ischemic Scale at study entry. Only about 50% of the patients had computerized tomography of the brain. For the subset designated as having Alzheimer's disease, a statistically significant treatment effect favoring Namenda over placebo at 12 weeks was seen on both the BGP and CGI-C.

INDICATIONS AND USAGE

Namenda (memantine hydrochloride) is indicated for the treatment of moderate to severe dementia of the Alzheimer's type.

CONTRAINDICATIONS

Namenda (memantine hydrochloride) is contraindicated in patients with known hypersensitivity to memantine hydrochloride or to any excipients used in the formulation.

PRECAUTIONS

Information for Patients and Caregivers: Caregivers should be instructed in the recommended administration (twice per day for doses above 5 mg) and dose escalation (minimum interval of one week between dose increases).

Neurological Conditions

Seizures: Namenda has not been systematically evaluated in patients with a seizure disorder. In clinical trials of Namenda, seizures occurred in 0.2% of patients treated with Namenda and 0.5% of patients treated with placebo.

Genitourinary Conditions

Conditions that raise urine pH may decrease the urinary elimination of memantine resulting in increased plasma levels of memantine.

Special Populations

Hepatic Impairment

Namenda undergoes partial hepatic metabolism, with about 48% of administered dose excreted in urine as unchanged drug or as the sum of parent drug and the N-glucuronide conjugate (74%). No dosage adjustment is needed in patients with mild or moderate hepatic impairment. Namenda should be administered with caution to patients with severe hepatic impairment.

Renal Impairment

No dosage adjustment is needed in patients with mild or moderate renal impairment. A dosage reduction is recommended in patients with severe renal impairment (see CLINICAL PHARMACOLOGY and DOSAGE AND ADMINISTRATION).

Drug-Drug Interactions

N-methyl-D-aspartate (NMDA) antagonists: The combined use of Namenda with other NMDA antagonists (amantadine, ketamine, and dextromethorphan) has not been systematically evaluated and such use should be approached with caution.

Effects of Namenda on substrates of microsomal enzymes: In vitro studies conducted with marker substrates of CYP450 enzymes (CYP1A2, -2A6, -2C9, -2D6, -2E1, -3A4) showed minimal inhibition of these enzymes by memantine. In addition, in vitro studies indicate that at concentrations exceeding those associated with efficacy, memantine does not induce the cytochrome P450 isozymes CYP1A2, CYP2C9, CYP2E1 and CYP3A4/5. No pharmacokinetic interactions with drugs metabolized by these enzymes are expected.

Effects of inhibitors and/or substrates of microsomal enzymes on Namenda: Memantine is predominantly renally eliminated, and drugs that are substrates and/or inhibitors of the CYP450 system are not expected to alter the metabolism of memantine.

Acetylcholinesterase (AChE) inhibitors: Coadministration of Namenda with the AChE inhibitor donepezil HCl did not affect the pharmacokinetics of either compound. In a 24-week controlled clinical study in patients with moderate to severe Alzheimer's disease, the adverse event profile observed with a combination of memantine and donepezil was similar to that of donepezil alone.

Drugs eliminated via renal mechanisms: Because memantine is eliminated in part by tubular secretion, coadministration of drugs that use the same renal cationic system, including hydrochlorothiazide (HCTZ), triamterene (TA), metformin, cimetidine, ranitidine, quinidine, and nicotine, could potentially result in altered plasma levels of both agents. However, coadministration of Namenda and HCTZ/TA did not affect the bioavailability of either memantine or TA, and the bioavailability of HCTZ decreased by 20%. In addition, coadministration of memantine with the antihyperglycemic drug Glucovance® (glyburide and metformin HCl) did not affect the pharmacokinetics of memantine, metformin and glyburide. Furthermore, memantine did not modify the serum glucose lowering effect of Glucovance®.

Drugs that make the urine alkaline: The clearance of memantine was reduced by about 80% under alkaline urine conditions at pH 8. Therefore, alterations of urine pH towards the alkaline condition may lead to an accumulation of the drug with a possible increase in adverse effects. Urine pH is altered by diet, drugs (e.g. carbonic anhydrase inhibitors, sodium bicarbonate) and clinical state of the patient (e.g. renal tubular acidosis or severe infections of the urinary tract). Hence, memantine should be used with caution under these conditions.

Carcinogenesis, Mutagenesis and Impairment of Fertility

There was no evidence of carcinogenicity in a 113-week oral study in mice at doses up to 40 mg/kg/day (10 times the maximum recommended human dose [MRHD] on a mg/m^2 basis). There was also no evidence of carcinogenicity in rats orally dosed at up to 40 mg/kg/day for 71 weeks followed by 20 mg/kg/day (20 and 10 times the MRHD on a mg/m^2 basis, respectively) through 128 weeks.

Memantine produced no evidence of genotoxic potential when evaluated in the in vitro S. typhimurium or E. coli reverse mutation assay, an in vitro chromosomal aberration test in human lymphocytes, an in vivo cytogenetics assay for chromosome damage in rats, and the in vivo mouse micronucleus assay. The results were equivocal in an in vitro gene mutation assay using Chinese hamster V79 cells.

No impairment of fertility or reproductive performance was seen in rats administered up to 18 mg/kg/day (9 times the MRHD on a mg/m^2 basis) orally from 14 days prior to mating through gestation and lactation in females, or for 60 days prior to mating in males.

Pregnancy

Pregnancy Category B: Memantine given orally to pregnant rats and pregnant rabbits during the period of organogenesis was not teratogenic up to the highest doses tested (18 mg/kg/day in rats and 30 mg/kg/day in rabbits, which are 9 and 30 times, respectively, the maximum recommended human dose [MRHD] on a mg/m^2 basis). Slight maternal toxicity, decreased pup weights and an increased incidence of non-ossified cervical vertebrae were seen at an oral dose of 18 mg/kg/day in a study in which rats were given oral memantine beginning pre-mating and continuing through the postpartum period. Slight maternal toxicity and decreased pup weights were also seen at this dose in a study in which rats were treated from day 15 of gestation through the post-partum period. The no-effect dose for these effects was 6 mg/kg, which is 3 times the MRHD on a mg/m^2 basis.

There are no adequate and well-controlled studies of memantine in pregnant women. Memantine should be used during pregnancy only if the potential benefit justifies the potential risk to the fetus.

Nursing Mothers

It is not known whether memantine is excreted in human breast milk. Because many drugs are excreted in human milk, caution should be exercised when memantine is administered to a nursing mother.

Pediatric Use

There are no adequate and well-controlled trials documenting the safety and efficacy of memantine in any illness occurring in children.

ADVERSE REACTIONS

The experience described in this section derives from studies in patients with Alzheimer's disease and vascular dementia.

Adverse Events Leading to Discontinuation: In placebo-controlled trials in which dementia patients received doses of Namenda up to 20 mg/day, the likelihood of discontinuation because of an adverse event was the same in the Namenda group as in the placebo group. No individual adverse event was associated with the discontinuation of treatment in 1% or more of Namenda-treated patients and at a rate greater than placebo.

Adverse Events Reported in Controlled Trials: The reported adverse events in Namenda (memantine hydrochloride) trials reflect experience gained under closely monitored conditions in a highly selected patient population. In actual practice or in other clinical trials, these frequency estimates may not apply, as the conditions of use, reporting behavior and the types of patients treated may differ. Table 1 lists treatment-emergent signs and symptoms that were reported in at least 2% of patients in placebo-controlled dementia trials and for which the rate of occurrence was greater for patients treated with Namenda than for those treated with placebo. No adverse event occurred at a frequency of at least 5% and twice the placebo rate.

Table 1: Adverse Events Reported in Controlled Clinical Trials in at Least 2% of Patients Receiving Namenda and at a Higher Frequency than Placebo-treated Patients.
Body System Adverse Event | Placebo (N = 922) % | Namenda (N = 940) %
Body as a Whole
Fatiuge | 1 | 2
Pain | 1 | 3
Cardiovascular System
Hypertension | 2 | 4
Central and Peripheral Nervous System
Dizziness | 5 | 7
Headache | 3 | 6
Gastrointestinal System
Constipation | 3 | 5
Vomiting | 2 | 3
Musculoskeletal System
Back pain | 2 | 3
Psychiatric Disorders
Confusion | 5 | 6
Somnolence | 2 | 3
Hallucination | 2 | 3
Respiratory System
Coughing | 3 | 4
Dyspnea | 1 | 2

Other adverse events occurring with an incidence of at least 2% in Namenda-treated patients but at a greater or equal rate on placebo were agitation, fall, inflicted injury, urinary incontinence, diarrhea, bronchitis, insomnia, urinary tract infection, influenza-like symptoms, abnormal gait, depression, upper respiratory tract infection, anxiety, peripheral edema, nausea, anorexia, and arthralgia.

The overall profile of adverse events and the incidence rates for individual adverse events in the subpopulation of patients with moderate to severe Alzheimer's disease were not different from the profile and incidence rates described above for the overall dementia population.

Vital Sign Changes: Namenda and placebo groups were compared with respect to (1) mean change from baseline in vital signs (pulse, systolic blood pressure, diastolic blood pressure, and weight) and (2) the incidence of patients meeting criteria for potentially clinically significant changes from baseline in these variables. There were no clinically important changes in vital signs in patients treated with Namenda. A comparison of supine and standing vital sign measures for Namenda and placebo in elderly normal subjects indicated that Namenda treatment is not associated with orthostatic changes.

Laboratory Changes: Namenda and placebo groups were compared with respect to (1) mean change from baseline in various serum chemistry, hematology, and urinalysis variables and (2) the incidence of patients meeting criteria for potentially clinically significant changes from baseline in these variables. These analyses revealed no clinically important changes in laboratory test parameters associated with Namenda treatment.

ECG Changes: Namenda and placebo groups were compared with respect to (1) mean change from baseline in various ECG parameters and (2) the incidence of patients meeting criteria for potentially clinically significant changes from baseline in these variables. These analyses revealed no clinically important changes in ECG parameters associated with Namenda treatment.

Other Adverse Events Observed During Clinical Trials

Namenda has been administered to approximately 1350 patients with dementia, of whom more than 1200 received the maximum recommended dose of 20 mg/day. Patients received Namenda treatment for periods of up to 884 days, with 862 patients receiving at least 24 weeks of treatment and 387 patients receiving 48 weeks or more of treatment.

Treatment emergent signs and symptoms that occurred during 8 controlled clinical trials and 4 open-label trials were recorded as adverse events by the clinical investigators using terminology of their own choosing. To provide an overall estimate of the proportion of individuals having similar types of events, the events were grouped into a smaller number of standardized categories using WHO terminology, and event frequencies were calculated across all studies.

All adverse events occurring in at least two patients are included, except for those already listed in Table 1, WHO terms too general to be informative, minor symptoms or events unlikely to be drug-caused, e.g., because they are common in the study population. Events are classified by body system and listed using the following definitions: frequent adverse events - those occurring in at least 1/100 patients; infrequent adverse events - those occurring in 1/100 to 1/1000 patients. These adverse events are not necessarily related to Namenda treatment and in most cases were observed at a similar frequency in placebo-treated patients in the controlled studies.

Body as a Whole: Frequent: syncope. Infrequent: hypothermia, allergic reaction.

Cardiovascular System: Frequent: cardiac failure. Infrequent: angina pectoris, bradycardia, myocardial infarction, thrombophlebitis, atrial fibrillation, hypotension, cardiac arrest, postural hypotension, pulmonary embolism, pulmonary edema.

Central and Peripheral Nervous System: Frequent: transient ischemic attack, cerebrovascular accident, vertigo, ataxia, hypokinesia. Infrequent: paresthesia, convulsions, extrapyramidal disorder, hypertonia, tremor, aphasia, hypoesthesia, abnormal coordination, hemiplegia, hyperkinesia, involuntary muscle contractions, stupor, cerebral hemorrhage, neuralgia, ptosis, neuropathy.

Gastrointestinal System: Infrequent: gastroenteritis, diverticulitis, gastrointestinal hemorrhage, melena, esophageal ulceration.

Hemic and Lymphatic Disorders: Frequent: anemia. Infrequent: leukopenia.

Metabolic and Nutritional Disorders: Frequent: increased alkaline phosphatase, decreased weight. Infrequent: dehydration, hyponatremia, aggravated diabetes mellitus.

Psychiatric Disorders: Frequent: aggressive reaction. Infrequent: delusion, personality disorder, emotional lability, nervousness, sleep disorder, libido increased, psychosis, amnesia, apathy, paranoid reaction, thinking abnormal, crying abnormal, appetite increased, paroniria, delirium, depersonalization, neurosis, suicide attempt.

Respiratory System: Frequent: pneumonia. Infrequent: apnea, asthma, hemoptysis.

Skin and Appendages: Frequent: rash. Infrequent: skin ulceration, pruritus, cellulitis, eczema, dermatitis, erythematous rash, alopecia, urticaria.

Special Senses: Frequent: cataract, conjunctivitis. Infrequent: macula lutea degeneration, decreased visual acuity, decreased hearing, tinnitus, blepharitis, blurred vision, corneal opacity, glaucoma, conjunctival hemorrhage, eye pain, retinal hemorrhage, xerophthalmia, diplopia, abnormal lacrimation, myopia, retinal detachment.

Urinary System: Frequent: frequent micturition. Infrequent: dysuria, hematuria, urinary retention.

Events Reported Subsequent to the Marketing of Namenda, both US and Ex-US

Although no causal relationship to memantine treatment has been found, the following adverse events have been reported to be temporally associated with memantine treatment and are not described elsewhere in labeling: aspiration pneumonia, asthenia, atrioventricular block, bone fracture, carpal tunnel syndrome, cerebral infarction, chest pain, cholelithiasis, claudication, colitis, deep venous thrombosis, depressed level of consciousness (including loss of consciousness and rare reports of coma), dyskinesia, dysphagia, encephalopathy, gastritis, gastroesophageal reflux, grand mal convulsions, intracranial hemorrhage, hepatitis (including increased ALT and AST and hepatic failure), hyperglycemia, hyperlipidemia, hypoglycemia, ileus, increased INR, impotence, lethargy, malaise, myoclonus, neuroleptic malignant syndrome, acute pancreatitis, Parkinsonism, acute renal failure (including increased creatinine and renal insufficiency), prolonged QT interval, restlessness, sepsis, Stevens-Johnson syndrome, suicidal ideation, sudden death, supraventricular tachycardia, tachycardia, tardive dyskinesia, thrombocytopenia, and hallucinations (both visual and auditory).

ANIMAL TOXICOLOGY

Memantine induced neuronal lesions (vacuolation and necrosis) in the multipolar and pyramidal cells in cortical layers III and IV of the posterior cingulate and retrosplenial neocortices in rats, similar to those which are known to occur in rodents administered other NMDA receptor antagonists. Lesions were seen after a single dose of memantine. In a study in which rats were given daily oral doses of memantine for 14 days, the no-effect dose for neuronal necrosis was 6 times the maximum recommended human dose on a mg/m^2 basis.The potential for induction of central neuronal vacuolation and necrosis by NMDA receptor antagonists in humans is unknown.

DRUG ABUSE AND DEPENDENCE

Controlled Substance Class: Memantine HCl is not a controlled substance.

Physical and Psychological Dependence: Memantine HCl is a low to moderate affinity uncompetitive NMDA antagonist that did not produce any evidence of drug-seeking behavior or withdrawal symptoms upon discontinuation in 2,504 patients who participated in clinical trials at therapeutic doses. Post marketing data, outside the U.S., retrospectively collected, has provided no evidence of drug abuse or dependence.

OVERDOSAGE

Signs and symptoms associated with memantine overdosage in clinical trials and from worldwide marketing experience include agitation, confusion, ECG changes, loss of consciousness, psychosis, restlessness, slowed movement, somnolence, stupor, unsteady gait, visual hallucinations, vertigo, vomiting, and weakness. The largest known ingestion of memantine worldwide was 2.0 grams in a patient who took memantine in conjunction with unspecified antidiabetic medications. The patient experienced coma, diplopia, and agitation, but subsequently recovered.

Because strategies for the management of overdose are continually evolving, it is advisable to contact a poison control center to determine the latest recommendations for the management of an overdose of any drug.

As in any cases of overdose, general supportive measures should be utilized, and treatment should be symptomatic. Elimination of memantine can be enhanced by acidification of urine.

DOSAGE AND ADMINISTRATION

The dosage of Namenda (memantine hydrochloride) shown to be effective in controlled clinical trials is 20 mg/day.

The recommended starting dose of Namenda is 5 mg once daily. The recommended target dose is 20 mg/day. The dose should be increased in 5 mg increments to 10 mg/day (5 mg twice a day), 15 mg/day (5 mg and 10 mg as separate doses), and 20 mg/day (10 mg twice a day). The minimum recommended interval between dose increases is one week.

Namenda can be taken with or without food.

Patients/caregivers should be instructed on how to use the Namenda Oral Solution dosing device. They should be made aware of the patient instruction sheet that is enclosed with the product. Patients/caregivers should be instructed to address any questions on the usage of the solution to their physician or pharmacist.

Doses in Special Populations

A target dose of 5 mg BID is recommended in patients with severe renal impairment (creatinine clearance of 5 – 29 mL/min based on the Cockroft-Gault equation):

For males: CLcr = [140-age (years)]· Weight (kg)/[72 · serum creatinine (mg/dL)]

For females: CLcr = 0.85 · [140-age (years)]· Weight (kg)/[72 · serum creatinine (mg/dL)]

HOW SUPPLIED

5 mg Tablet:

Bottle of 60 | NDC #21695-232-60

The capsule-shaped, film-coated tablets are tan, with the strength (5) debossed on one side and FL on the other.

10 mg Tablet:

Bottle of 30 | NDC #21695-169-30
Bottle of 60 | NDC #21695-169-60

The capsule-shaped, film-coated tablets are gray, with the strength (10) debossed on one side and FL on the other.

Repackaged by

Rebel Distributors Corp

Thousand Oaks, CA 91320